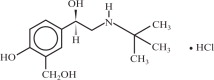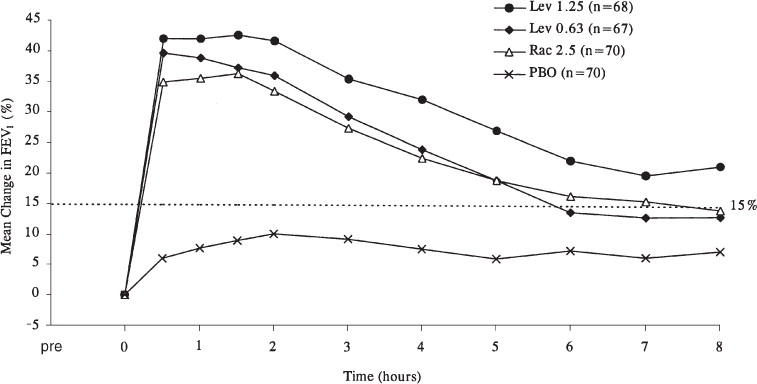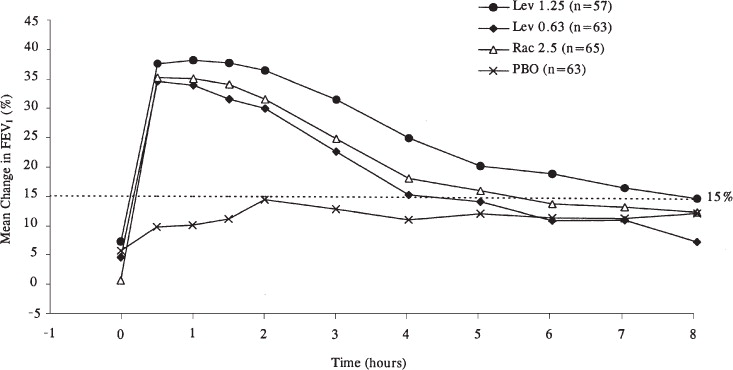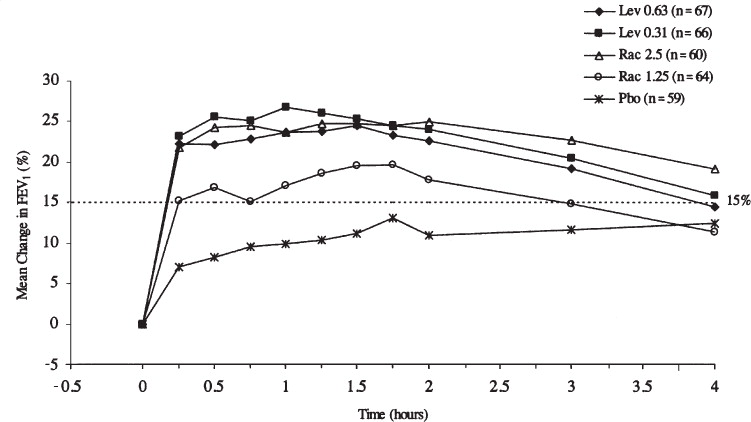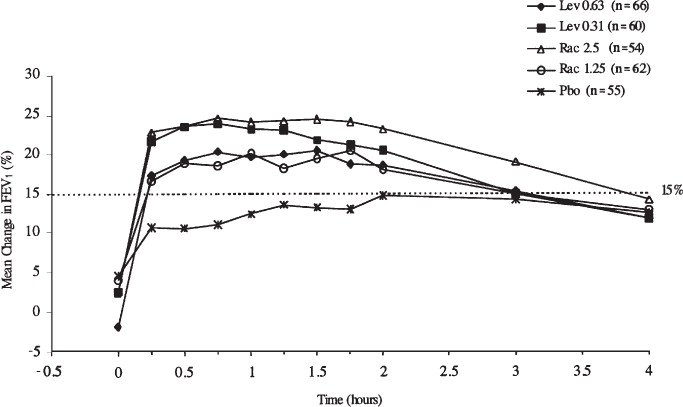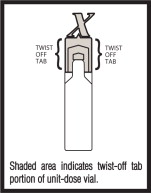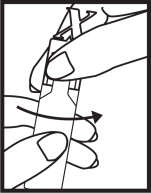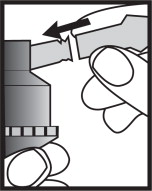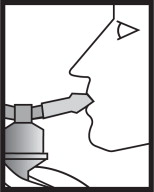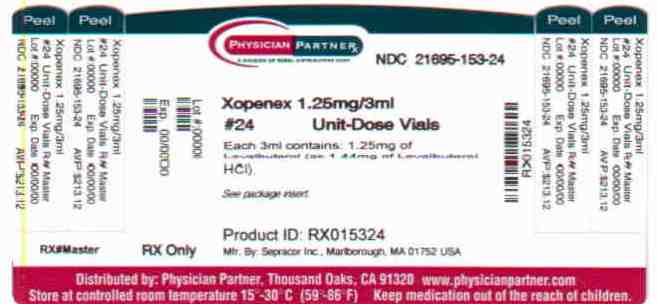 DRUG LABEL: Xopenex
NDC: 21695-153 | Form: SOLUTION
Manufacturer: Rebel Distributors Corp
Category: prescription | Type: HUMAN PRESCRIPTION DRUG LABEL
Date: 20101201

ACTIVE INGREDIENTS: levalbuterol hydrochloride 1.25 mg/3 mL
INACTIVE INGREDIENTS: sodium chloride; sulfuric acid; water; nitrogen

Xopenex® (levalbuterol HCl) Inhalation Solution
0.31 mg*, 0.63 mg*, 1.25 mg*

*Potency expressed as levalbuterol

PRESCRIBING INFORMATION

DESCRIPTION:

Xopenex (levalbuterol HCl) Inhalation Solution is a sterile, clear, colorless, preservative-free solution of the hydrochloride salt of levalbuterol, the (R)-enantiomer of the drug substance racemic albuterol. Levalbuterol HCl is a relatively selective beta2-adrenergic receptor agonist (see CLINICAL PHARMACOLOGY). The chemical name for levalbuterol HCl is (R)-α^1-[[(1,1-dimethylethyl)amino]methyl]-4-hydroxy-1,3-benzenedimethanol hydrochloride, and its established chemical structure is as follows:

The molecular weight of levalbuterol HCl is 275.8, and its empirical formula is C13H21NO3•HCl. It is a white to off-white, crystalline solid, with a melting point of approximately 187°C and solubility of approximately 180 mg/mL in water.

Levalbuterol HCl is the USAN modified name for (R)-albuterol HCl in the United States.

Xopenex (levalbuterol HCl) Inhalation Solution is supplied in unit-dose vials and requires no dilution before administration by nebulization. Each 3 mL unit-dose vial contains 0.31 mg of levalbuterol (as 0.36 mg of levalbuterol HCl) or 0.63 mg of levalbuterol (as 0.73 mg of levalbuterol HCl) or 1.25 mg of levalbuterol (as 1.44 mg of levalbuterol HCl), sodium chloride to adjust tonicity, and sulfuric acid to adjust the pH to 4.0 (3.3 to 4.5).

CLINICAL PHARMACOLOGY:

Activation of beta2-adrenergic receptors on airway smooth muscle leads to the activation of adenylcyclase and to an increase in the intracellular concentration of cyclic-3´, 5´-adenosine monophosphate (cyclic AMP). This increase in cyclic AMP leads to the activation of protein kinase A, which inhibits the phosphorylation of myosin and lowers intracellular ionic calcium concentrations, resulting in relaxation. Levalbuterol relaxes the smooth muscles of all airways, from the trachea to the terminal bronchioles. Levalbuterol acts as a functional antagonist to relax the airway irrespective of the spasmogen involved, thus protecting against all bronchoconstrictor challenges. Increased cyclic AMP concentrations are also associated with the inhibition of release of mediators from mast cells in the airway.

While it is recognized that beta2-adrenergic receptors are the predominant receptors on bronchial smooth muscle, data indicate that there is a population of beta2-receptors in the human heart that comprise between 10% and 50% of cardiac beta-adrenergic receptors. The precise function of these receptors has not been established (see WARNINGS). However, all beta-adrenergic agonist drugs can produce a significant cardiovascular effect in some patients, as measured by pulse rate, blood pressure, symptoms, and/or electrocardiographic changes.

Preclinical Studies

Results from an in vitro study of binding to human beta-adrenergic receptors demonstrated that levalbuterol has approximately 2-fold greater binding affinity than racemic albuterol and approximately 100-fold greater binding affinity than (S)-albuterol. In guinea pig airways, levalbuterol HCl and racemic albuterol decreased the response to spasmogens (e.g., acetylcholine and histamine), whereas (S)-albuterol was ineffective. These results suggest that the bronchodilatory effects of racemic albuterol are attributable to the (R)-enantiomer.

Intravenous studies in rats with racemic albuterol sulfate have demonstrated that albuterol crosses the blood-brain barrier and reaches brain concentrations amounting to approximately 5.0% of the plasma concentrations. In structures outside the blood-brain barrier (pineal and pituitary glands), albuterol concentrations were found to be 100 times those in the whole brain.

Studies in laboratory animals (minipigs, rodents, and dogs) have demonstrated the occurrence of cardiac arrhythmias and sudden death (with histologic evidence of myocardial necrosis) when beta-agonists and methylxanthines are administered concurrently. The clinical significance of these findings is unknown.

Pharmacokinetics (Adults And Adolescents ≥12 Years Old)

The inhalation pharmacokinetics of Xopenex Inhalation Solution were investigated in a randomized cross-over study in 30 healthy adults following administration of a single dose of 1.25 mg and a cumulative dose of 5 mg of Xopenex Inhalation Solution and a single dose of 2.5 mg and a cumulative dose of 10 mg of racemic albuterol sulfate inhalation solution by nebulization using a PARI LC Jet™ nebulizer with a Dura-Neb® 2000 compressor.

Following administration of a single 1.25 mg dose of Xopenex Inhalation Solution, exposure to (R)-albuterol (AUC of 3.3 ng•hr/mL) was approximately 2-fold higher than following administration of a single 2.5 mg dose of racemic albuterol inhalation solution (AUC of 1.7 ng•hr/mL) (see Table 1). Following administration of a cumulative 5 mg dose of Xopenex Inhalation Solution (1.25 mg given every 30 minutes for a total of four doses) or a cumulative 10 mg dose of racemic albuterol inhalation solution (2.5 mg given every 30 minutes for a total of four doses), Cmax and AUC of (R)-albuterol were comparable (see Table 1).

Table 1: Mean (SD) Values for Pharmacokinetic Parameters in Healthy Adults
 |  | Single Dose |  |  | Cumulative Dose
 |  | Xopenex 1.25 mg | Racemic albuterol sulfate 2.5 mg |  | Xopenex 5 mg | Racemic albuterol sulfate 10 mg
Cmax (ng/mL)
(R)-albuterol |  | 1.1 (0.45) | 0.8 (0.41)** |  | 4.5 (2.20) | 4.2 (1.51)**
Tmax (h)γ
(R)-albuterol |  | 0.2 (0.17, 0.37) | 0.2 (0.17, 1.50) |  | 0.2 (–0.18*, 1.25) | 0.2 (–0.28*, 1.00)
AUC (ng•h/mL)
(R)-albuterol |  | 3.3 (1.58) | 1.7 (0.99)** |  | 17.4 (8.56) | 16.0 (7.12)**
T½ (h)
(R)-albuterol |  | 3.3 (2.48) | 1.5 (0.61) |  | 4.0 (1.05) | 4.1 (0.97)
γ Median (Min, Max) reported for Tmax.
* A negative Tmax indicates Cmax occurred between first and last nebulizations.
** Values reflect only (R)-albuterol and do not include (S)-albuterol.

Pharmacokinetics (Children 6–11 Years Old)

The pharmacokinetic parameters of (R)- and (S)-albuterol in children with asthma were obtained using population pharmacokinetic analysis. These data are presented in Table 2. For comparison, adult data obtained by conventional pharmacokinetic analysis from a different study also are presented in Table 2.

In children, AUC and Cmax of (R)-albuterol following administration of 0.63 mg Xopenex Inhalation Solution were comparable to those following administration of 1.25 mg racemic albuterol sulfate inhalation solution.

When the same dose of 0.63 mg of Xopenex was given to children and adults, the predicted Cmax of (R)–albuterol in children was similar to that in adults (0.52 vs. 0.56 ng/mL), while predicted AUC in children (2.55 ng•hr/mL) was about 1.5-fold higher than that in adults (1.65 ng•hr/mL). These data support lower doses for children 6-11 years old compared with the adult doses (see DOSAGE AND ADMINISTRATION).

Table 2: (R)-Albuterol Exposure in Adults and Pediatric Subjects (6-11 years)
 | Children 6-11 years |  |  |  |  | Adults ≥12 years
Treatment | Xopenex 0.31 mg | Xopenex 0.63 mg | Racemic albuterol 1.25mg | Racemic albuterol 2.5 mg |  | Xopenex 0.63 mg | Xopenex 1.25 mg
AUC0-∞ (ng•hr/mL) c | 1.36 | 2.55 | 2.65 | 5.02 |  | 1.65 a | 3.3 b
Cmax (ng/mL) d | 0.303 | 0.521 | 0.553 | 1.08 |  | 0.56 a | 1.1 b
a The values are predicted by assuming linear pharmacokinetics
b The data obtained from Table 1
c Area under the plasma concentration curve from time 0 to infinity
d Maximum plasma concentration

Metabolism and Elimination

Information available in the published literature suggests that the primary enzyme responsible for the metabolism of albuterol enantiomers in humans is SULT1A3 (sulfotransferase). When racemic albuterol was administered either intravenously or via inhalation after oral charcoal administration, there was a 3- to 4-fold difference in the area under the concentration-time curves between the (R)- and (S)-albuterol enantiomers, with (S)-albuterol concentrations being consistently higher. However, without charcoal pretreatment, after either oral or inhalation administration the differences were 8- to 24-fold, suggesting that (R)-albuterol is preferentially metabolized in the gastrointestinal tract, presumably by SULT1A3.

The primary route of elimination of albuterol enantiomers is through renal excretion (80% to 100%) of either the parent compound or the primary metabolite. Less than 20% of the drug is detected in the feces. Following intravenous administration of racemic albuterol, between 25% and 46% of the (R)-albuterol fraction of the dose was excreted as unchanged (R)-albuterol in the urine.

Special Populations

Hepatic Impairment: The effect of hepatic impairment on the pharmacokinetics of Xopenex Inhalation Solution has not been evaluated.

Renal Impairment: The effect of renal impairment on the pharmacokinetics of racemic albuterol was evaluated in 5 subjects with creatinine clearance of 7 to 53 mL/min, and the results were compared with those from healthy volunteers. Renal disease had no effect on the half-life, but there was a 67% decline in racemic albuterol clearance. Caution should be used when administering high doses of Xopenex Inhalation Solution to patients with renal impairment.

Pharmacodynamics (Adults And Adolescents ≥12 Years Old)

In a randomized, double-blind, placebo-controlled, cross-over study, 20 adults with mild-to-moderate asthma received single doses of Xopenex Inhalation Solution (0.31, 0.63, and 1.25 mg) and racemic albuterol sulfate inhalation solution (2.5 mg). All doses of active treatment produced a significantly greater degree of bronchodilation (as measured by percent change from pre-dose mean FEV1) than placebo, and there were no significant differences between any of the active treatment arms. The bronchodilator responses to 1.25 mg of Xopenex Inhalation Solution and 2.5 mg of racemic albuterol sulfate inhalation solution were clinically comparable over the 6-hour evaluation period, except for a slightly longer duration of action (>15% increase in FEV1 from baseline) after administration of 1.25 mg of Xopenex Inhalation Solution. Systemic beta-adrenergic adverse effects were observed with all active doses and were generally dose-related for (R)-albuterol. Xopenex Inhalation Solution at a dose of 1.25 mg produced a slightly higher rate of systemic beta-adrenergic adverse effects than the 2.5 mg dose of racemic albuterol sulfate inhalation solution.

In a randomized, double-blind, placebo-controlled, cross-over study, 12 adults with mild-to-moderate asthma were challenged with inhaled methacholine chloride 20 and 180 minutes following administration of a single dose of 2.5 mg of racemic albuterol sulfate, 1.25 mg of Xopenex, 1.25 mg of (S)-albuterol, or placebo using a PARI LC Jet™ nebulizer. Racemic albuterol sulfate, Xopenex, and (S)-albuterol had a protective effect against methacholine-induced bronchoconstriction 20 minutes after administration, although the effect of (S)-albuterol was minimal. At 180 minutes after administration, the bronchoprotective effect of 1.25 mg of Xopenex was comparable to that of 2.5 mg of racemic albuterol sulfate. At 180 minutes after administration, 1.25 mg of (S)-albuterol had no bronchoprotective effect.

In a clinical study in adults with mild-to-moderate asthma, comparable efficacy (as measured by change from baseline FEV1) and safety (as measured by heart rate, blood pressure, ECG, serum potassium, and tremor) were demonstrated after a cumulative dose of 5 mg of Xopenex Inhalation Solution (four consecutive doses of 1.25 mg administered every 30 minutes) and 10 mg of racemic albuterol sulfate inhalation solution (four consecutive doses of 2.5 mg administered every 30 minutes).

Clinical Trials (Adults And Adolescents ≥12 Years Old)

The safety and efficacy of Xopenex Inhalation Solution were evaluated in a 4-week, multicenter, randomized, double-blind, placebo-controlled, parallel-group study in 362 adult and adolescent patients 12 years of age and older, with mild-to-moderate asthma (mean baseline FEV1 60% of predicted). Approximately half of the patients were also receiving inhaled corticosteroids. Patients were randomized to receive Xopenex 0.63 mg, Xopenex 1.25 mg, racemic albuterol sulfate 1.25 mg, racemic albuterol sulfate 2.5 mg, or placebo three times a day administered via a PARI LC Plus™ nebulizer and a Dura-Neb® portable compressor. Racemic albuterol delivered by a chlorofluorocarbon (CFC) metered dose inhaler (MDI) was used on an as-needed basis as the rescue medication.

Efficacy, as measured by the mean percent change from baseline FEV1, was demonstrated for all active treatment regimens compared with placebo on day 1 and day 29. On both day 1 (see Figure 1) and day 29 (see Figure 2), 1.25 mg of Xopenex demonstrated the largest mean percent change from baseline FEV1 compared with the other active treatments. A dose of 0.63 mg of Xopenex and 2.5 mg of racemic albuterol sulfate produced a clinically comparable mean percent change from baseline FEV1 on both day 1 and day 29.

Figure 1: Mean Percent Change from Baseline FEV1 on Day 1, Adults and Adolescents ≥12 years old

Figure 2: Mean Percent Change from Baseline FEV1 on Day 29, Adults and Adolescents ≥12 years old

The mean time to onset of a 15% increase in FEV1 over baseline for levalbuterol at doses of 0.63 mg and 1.25 mg was approximately 17 minutes and 10 minutes, respectively, and the mean time to peak effect for both doses was approximately 1.5 hours after 4 weeks of treatment. The mean duration of effect, as measured by a >15% increase from baseline FEV1, was approximately 5 hours after administration of 0.63 mg of levalbuterol and approximately 6 hours after administration of 1.25 mg of levalbuterol after 4 weeks of treatment. In some patients, the duration of effect was as long as 8 hours.

Clinical Trials (Children 6–11 Years Old)

A multi-center, randomized, double-blind, placebo- and active-controlled study was conducted in children with mild-to-moderate asthma (mean baseline FEV1 73% of predicted) (n=316). Following a 1-week placebo run-in, subjects were randomized to Xopenex (0.31 or 0.63 mg), racemic albuterol (1.25 or 2.5 mg), or placebo, which were delivered three times a day for 3 weeks using a PARI LC Plus™ nebulizer and a Dura-Neb® 3000 compressor.

Efficacy, as measured by mean peak percent change from baseline FEV1, was demonstrated for all active treatment regimens compared with placebo on day 1 and day 21. Time profile FEV1 curves for day 1 and day 21 are shown in Figure 3 and Figure 4, respectively. The onset of effect (time to a 15% increase in FEV1 over test-day baseline) and duration of effect (maintenance of a >15% increase in FEV1 over test-day baseline) of levalbuterol were clinically comparable to those of racemic albuterol.

Figure 3: Mean Percent Change from Baseline FEV1 on Day 1, Children 6-11 Years of Age

Figure 4: Mean Percent Change from Baseline FEV1 on Day 21, Children 6-11 Years of Age

INDICATIONS AND USAGE:

Xopenex (levalbuterol HCl) Inhalation Solution is indicated for the treatment or prevention of bronchospasm in adults, adolescents, and children 6 years of age and older with reversible obstructive airway disease.

CONTRAINDICATIONS:

Xopenex (levalbuterol HCl) Inhalation Solution is contraindicated in patients with a history of hypersensitivity to levalbuterol HCl or racemic albuterol.

WARNINGS:

1. Paradoxical Bronchospasm: Like other inhaled beta-adrenergic agonists, Xopenex Inhalation Solution can produce paradoxical bronchospasm, which may be life threatening. If paradoxical bronchospasm occurs, Xopenex Inhalation Solution should be discontinued immediately and alternative therapy instituted. It should be recognized that paradoxical bronchospasm, when associated with inhaled formulations, frequently occurs with the first use of a new canister or vial.
2. Deterioration of Asthma: Asthma may deteriorate acutely over a period of hours or chronically over several days or longer. If the patient needs more doses of Xopenex Inhalation Solution than usual, this may be a marker of destabilization of asthma and requires reevaluation of the patient and treatment regimen, giving special consideration to the possible need for anti-inflammatory treatment, e.g., corticosteroids.
3. Use of Anti-Inflammatory Agents: The use of beta-adrenergic agonist bronchodilators alone may not be adequate to control asthma in many patients. Early consideration should be given to adding anti-inflammatory agents, e.g., corticosteroids, to the therapeutic regimen.
4. Cardiovascular Effects: Xopenex Inhalation Solution, like all other beta-adrenergic agonists, can produce a clinically significant cardiovascular effect in some patients, as measured by pulse rate, blood pressure, and/or symptoms. Although such effects are uncommon after administration of Xopenex Inhalation Solution at recommended doses, if they occur, the drug may need to be discontinued. In addition, beta-agonists have been reported to produce ECG changes, such as flattening of the T wave, prolongation of the QTc interval, and ST segment depression. The clinical significance of these findings is unknown. Therefore, Xopenex Inhalation Solution, like all sympathomimetic amines, should be used with caution in patients with cardiovascular disorders, especially coronary insufficiency, cardiac arrhythmias, and hypertension.
5. Do Not Exceed Recommended Dose: Fatalities have been reported in association with excessive use of inhaled sympathomimetic drugs in patients with asthma. The exact cause of death is unknown, but cardiac arrest following an unexpected development of a severe acute asthmatic crisis and subsequent hypoxia is suspected.
6. Immediate Hypersensitivity Reactions: Immediate hypersensitivity reactions may occur after administration of racemic albuterol, as demonstrated by rare cases of urticaria, angioedema, rash, bronchospasm, anaphylaxis, and oropharyngeal edema. The potential for hypersensitivity must be considered in the clinical evaluation of patients who experience immediate hypersensitivity reactions while receiving Xopenex Inhalation Solution.

PRECAUTIONS:

General

Levalbuterol HCl, like all sympathomimetic amines, should be used with caution in patients with cardiovascular disorders, especially coronary insufficiency, hypertension, and cardiac arrhythmias; in patients with convulsive disorders, hyperthyroidism, or diabetes mellitus; and in patients who are unusually responsive to sympathomimetic amines. Clinically significant changes in systolic and diastolic blood pressure have been seen in individual patients and could be expected to occur in some patients after the use of any beta-adrenergic bronchodilator.

Large doses of intravenous racemic albuterol have been reported to aggravate preexisting diabetes mellitus and ketoacidosis. As with other beta-adrenergic agonist medications, levalbuterol may produce significant hypokalemia in some patients, possibly through intracellular shunting, which has the potential to produce adverse cardiovascular effects. The decrease is usually transient, not requiring supplementation.

Information For Patients

See illustrated Patient's Instructions for Use.

The action of Xopenex (levalbuterol HCl) Inhalation Solution may last up to 8 hours. Xopenex Inhalation Solution should not be used more frequently than recommended. Do not increase the dose or frequency of dosing of Xopenex Inhalation Solution without consulting your physician. If you find that treatment with Xopenex Inhalation Solution becomes less effective for symptomatic relief, your symptoms become worse, and/or you need to use the product more frequently than usual, you should seek medical attention immediately. While you are taking Xopenex Inhalation Solution, other inhaled drugs and asthma medications should be taken only as directed by your physician. Common adverse effects include palpitations, chest pain, rapid heart rate, headache, dizziness, and tremor or nervousness. If you are pregnant or nursing, contact your physician about the use of Xopenex Inhalation Solution.

Effective and safe use of Xopenex Inhalation Solution requires consideration of the following information in addition to that provided under Patient's Instructions for Use:

Xopenex Inhalation Solution single-use low-density polyethylene (LDPE) vials should be protected from light and excessive heat. Store in the protective foil pouch between 20°C and 25°C (68°F and 77°F) [see USP Controlled Room Temperature]. Do not use after the expiration date stamped on the container. Unused vials should be stored in the protective foil pouch. Once the foil pouch is opened, the vials should be used within 2 weeks. Vials removed from the pouch, if not used immediately, should be protected from light and used within 1 week. Discard any vial if the solution is not colorless.

The drug compatibility (physical and chemical), efficacy, and safety of Xopenex Inhalation Solution when mixed with other drugs in a nebulizer have not been established.

Drug Interactions

Other short-acting sympathomimetic aerosol bronchodilators or epinephrine should be used with caution with levalbuterol. If additional adrenergic drugs are to be administered by any route, they should be used with caution to avoid deleterious cardiovascular effects.

1. Beta-blockers: Beta-adrenergic receptor blocking agents not only block the pulmonary effect of beta-agonists such as Xopenex (levalbuterol HCl) Inhalation Solution, but may also produce severe bronchospasm in asthmatic patients. Therefore, patients with asthma should not normally be treated with beta-blockers. However, under certain circumstances, e.g., prophylaxis after myocardial infarction, there may be no acceptable alternatives to the use of beta-adrenergic blocking agents in patients with asthma. In this setting, cardioselective beta-blockers could be considered, although they should be administered with caution.
2. Diuretics: The ECG changes and/or hypokalemia that may result from the administration of non-potassium sparing diuretics (such as loop or thiazide diuretics) can be acutely worsened by beta-agonists, especially when the recommended dose of the beta-agonist is exceeded. Although the clinical significance of these effects is not known, caution is advised in the coadministration of beta-agonists with non-potassium sparing diuretics.
3. Digoxin: Mean decreases of 16% and 22% in serum digoxin levels were demonstrated after single-dose intravenous and oral administration of racemic albuterol, respectively, to normal volunteers who had received digoxin for 10 days. The clinical significance of these findings for patients with obstructive airway disease who are receiving levalbuterol HCl and digoxin on a chronic basis is unclear. Nevertheless, it would be prudent to carefully evaluate the serum digoxin levels in patients who are currently receiving digoxin and Xopenex Inhalation Solution.
4. Monoamine Oxidase Inhibitors or Tricyclic Antidepressants: Xopenex Inhalation Solution should be administered with extreme caution to patients being treated with monoamine oxidase inhibitors or tricyclic antidepressants, or within 2 weeks of discontinuation of such agents, because the action of levalbuterol HCl on the vascular system may be potentiated.

Carcinogenesis, Mutagenesis, And Impairment Of Fertility

No carcinogenesis or impairment of fertility studies have been carried out with levalbuterol HCl alone. However, racemic albuterol sulfate has been evaluated for its carcinogenic potential and ability to impair fertility.

In a 2-year study in Sprague-Dawley rats, racemic albuterol sulfate caused a significant dose-related increase in the incidence of benign leiomyomas of the mesovarium at and above dietary doses of 2 mg/kg (approximately 2 times the maximum recommended daily inhalation dose of levalbuterol HCl for adults and children on a mg/m^2 basis). In another study, this effect was blocked by the coadministration of propranolol, a nonselective beta-adrenergic antagonist. In an 18-month study in CD-1 mice, racemic albuterol sulfate showed no evidence of tumorigenicity at dietary doses up to 500 mg/kg (approximately 260 times the maximum recommended daily inhalation dose of levalbuterol HCl for adults and children on a mg/m^2 basis). In a 22-month study in the Golden hamster, racemic albuterol sulfate showed no evidence of tumorigenicity at dietary doses up to 50 mg/kg (approximately 35 times the maximum recommended daily inhalation dose of levalbuterol HCl for adults and children on a mg/m^2 basis).

Levalbuterol HCl was not mutagenic in the Ames test or the CHO/HPRT Mammalian Forward Gene Mutation Assay. Although levalbuterol HCl has not been tested for clastogenicity, racemic albuterol sulfate was not clastogenic in a human peripheral lymphocyte assay or in an AH1 strain mouse micronucleus assay. Reproduction studies in rats using racemic albuterol sulfate demonstrated no evidence of impaired fertility at oral doses up to 50 mg/kg (approximately 55 times the maximum recommended daily inhalation dose of levalbuterol HCl for adults on a mg/m^2 basis).

Teratogenic Effects — Pregnancy Category C

A reproduction study in New Zealand White rabbits demonstrated that levalbuterol HCl was not teratogenic when administered orally at doses up to 25 mg/kg (approximately 110 times the maximum recommended daily inhalation dose of levalbuterol HCl for adults on a mg/m^2 basis). However, racemic albuterol sulfate has been shown to be teratogenic in mice and rabbits. A study in CD-1 mice given racemic albuterol sulfate subcutaneously showed cleft palate formation in 5 of 111 (4.5%) fetuses at 0.25 mg/kg (less than the maximum recommended daily inhalation dose of levalbuterol HCl for adults on a mg/m^2 basis) and in 10 of 108 (9.3%) fetuses at 2.5 mg/kg (approximately equal to the maximum recommended daily inhalation dose of levalbuterol HCl for adults on a mg/m^2 basis). The drug did not induce cleft palate formation when administered subcutaneously at a dose of 0.025 mg/kg (less than the maximum recommended daily inhalation dose of levalbuterol HCl for adults on a mg/m^2 basis). Cleft palate also occurred in 22 of 72 (30.5%) fetuses from females treated subcutaneously with 2.5 mg/kg of isoproterenol (positive control).

A reproduction study in Stride Dutch rabbits revealed cranioschisis in 7 of 19 (37%) fetuses when racemic albuterol sulfate was administered orally at a dose of 50 mg/kg (approximately 110 times the maximum recommended daily inhalation dose of levalbuterol HCl for adults on a mg/m^2 basis).

A study in which pregnant rats were dosed with radiolabeled racemic albuterol sulfate demonstrated that drug-related material is transferred from the maternal circulation to the fetus.

There are no adequate and well-controlled studies of Xopenex Inhalation Solution in pregnant women. Because animal reproduction studies are not always predictive of human response, Xopenex Inhalation Solution should be used during pregnancy only if the potential benefit justifies the potential risk to the fetus.

During marketing experience of racemic albuterol, various congenital anomalies, including cleft palate and limb defects, have been rarely reported in the offspring of patients being treated with racemic albuterol. Some of the mothers were taking multiple medications during their pregnancies. No consistent pattern of defects can be discerned, and a relationship between racemic albuterol use and congenital anomalies has not been established.

Use In Labor And Delivery

Because of the potential for beta-adrenergic agonists to interfere with uterine contractility, the use of Xopenex Inhalation Solution for the treatment of bronchospasm during labor should be restricted to those patients in whom the benefits clearly outweigh the risk.

Tocolysis

Levalbuterol HCl has not been approved for the management of preterm labor. The benefit:risk ratio when levalbuterol HCl is administered for tocolysis has not been established. Serious adverse reactions, including maternal pulmonary edema, have been reported during or following treatment of premature labor with beta2-agonists, including racemic albuterol.

Nursing Mothers

Plasma levels of levalbuterol after inhalation of therapeutic doses are very low in humans, but it is not known whether levalbuterol is excreted in human milk.

Because of the potential for tumorigenicity shown for racemic albuterol in animal studies and the lack of experience with the use of Xopenex Inhalation Solution by nursing mothers, a decision should be made whether to discontinue nursing or to discontinue the drug, taking into account the importance of the drug to the mother. Caution should be exercised when Xopenex Inhalation Solution is administered to a nursing woman.

Pediatrics

The safety and efficacy of Xopenex (levalbuterol HCl) Inhalation Solution have been established in pediatric patients 6 years of age and older in one adequate and well-controlled clinical trial (see CLINICAL PHARMACOLOGY; Pharmacokinetics and Clinical Trials). Use of Xopenex in children is also supported by evidence from adequate and well-controlled studies of Xopenex in adults, considering that the pathophysiology and the drug's exposure level and effects in pediatric and adult patients are substantially similar. Safety and effectiveness of Xopenex in pediatric patients below the age of 6 years have not been established.

Geriatrics

Data on the use of Xopenex in patients 65 years of age and older are very limited. A very small number of patients 65 years of age and older were treated with Xopenex Inhalation Solution in a 4-week clinical study (see CLINICAL PHARMACOLOGY; Clinical Trials) (n=2 for 0.63 mg and n=3 for 1.25 mg). In these patients, bronchodilation was observed after the first dose on day 1 and after 4 weeks of treatment. There are insufficient data to determine if the safety and efficacy of Xopenex Inhalation Solution are different in patients < 65 years of age and patients 65 years of age and older. In general, patients 65 years of age and older should be started at a dose of 0.63 mg of Xopenex Inhalation Solution. If clinically warranted due to insufficient bronchodilator response, the dose of Xopenex Inhalation Solution may be increased in elderly patients as tolerated, in conjunction with frequent clinical and laboratory monitoring, to the maximum recommended daily dose (see DOSAGE AND ADMINISTRATION).

ADVERSE REACTIONS (ADULTS AND ADOLESCENTS ≥12 YEARS OLD):

Adverse events reported in ≥2% of patients receiving Xopenex Inhalation Solution or racemic albuterol and more frequently than in patients receiving placebo in a 4-week, controlled clinical trial are listed in Table 3.

Table 3: Adverse Events Reported in a 4-Week, Controlled Clinical Trial in Adults and Adolescents ≥12 years old
 | Percent of Patients
Body System Preferred Term | Placebo (n=75) | Xopenex 1.25 mg (n=73) | Xopenex 0.63 mg (n=72) | Racemic albuterol 2.5 mg (n=74)
Body as a Whole
Allergic reaction | 1.3 | 0 | 0 | 2.7
Flu syndrome | 0 | 1.4 | 4.2 | 2.7
Accidental injury | 0 | 2.7 | 0 | 0
Pain | 1.3 | 1.4 | 2.8 | 2.7
Back pain | 0 | 0 | 0 | 2.7
Cardiovascular System
Tachycardia | 0 | 2.7 | 2.8 | 2.7
Migraine | 0 | 2.7 | 0 | 0
Digestive System
Dyspepsia | 1.3 | 2.7 | 1.4 | 1.4
Musculoskeletal System
Leg cramps | 1.3 | 2.7 | 0 | 1.4
Central Nervous System
Dizziness | 1.3 | 2.7 | 1.4 | 0
Hypertonia | 0 | 0 | 0 | 2.7
Nervousness | 0 | 9.6 | 2.8 | 8.1
Tremor | 0 | 6.8 | 0 | 2.7
Anxiety | 0 | 2.7 | 0 | 0
Respiratory System
Cough increased | 2.7 | 4.1 | 1.4 | 2.7
Infection viral | 9.3 | 12.3 | 6.9 | 12.2
Rhinitis | 2.7 | 2.7 | 11.1 | 6.8
Sinusitis | 2.7 | 1.4 | 4.2 | 2.7
Turbinate edema | 0 | 1.4 | 2.8 | 0

The incidence of certain systemic beta-adrenergic adverse effects (e.g., tremor, nervousness) was slightly less in the Xopenex 0.63 mg group compared with the other active treatment groups. The clinical significance of these small differences is unknown.

Changes in heart rate 15 minutes after drug administration and in plasma glucose and potassium 1 hour after drug administration on day 1 and day 29 were clinically comparable in the Xopenex 1.25 mg and racemic albuterol 2.5 mg groups (see Table 4). Changes in heart rate and plasma glucose were slightly less in the Xopenex 0.63 mg group compared with the other active treatment groups (see Table 4). The clinical significance of these small differences is unknown. After 4 weeks, effects on heart rate, plasma glucose, and plasma potassium were generally diminished compared with day 1 in all active treatment groups.

Table 4: Mean Changes from Baseline Heart Rate at 15 Minutes and Glucose and Potassium at 1 Hour after First Dose (Day 1) in Adults and Adolescents ≥12 years old
Treatment | Mean Changes (day 1)
Treatment | Heart Rate (bpm) | Glucose (mg/dL) | Potassium (mEq/L)
Xopenex 0.63 mg, n=72 | 2.4 | 4.6 | –0.2
Xopenex 1.25 mg, n=73 | 6.9 | 10.3 | –0.3
Racemic albuterol 2.5 mg, n=74 | 5.7 | 8.2 | –0.3
Placebo, n=75 | –2.8 | –0.2 | –0.2

No other clinically relevant laboratory abnormalities related to administration of Xopenex Inhalation Solution were observed in this study.

In the clinical trials, a slightly greater number of serious adverse events, discontinuations due to adverse events, and clinically significant ECG changes were reported in patients who received Xopenex 1.25 mg compared with the other active treatment groups.

The following adverse events, considered potentially related to Xopenex, occurred in less than 2% of the 292 subjects who received Xopenex and more frequently than in patients who received placebo in any clinical trial:

Body as a Whole: | chills, pain, chest pain
Cardiovascular System: | ECG abnormal, ECG change, hypertension,
 | hypotension, syncope
Digestive System: | diarrhea, dry mouth, dry throat, dyspepsia, gastroenteritis, nausea
Hemic and Lymphatic System: | lymphadenopathy
Musculoskeletal System: | leg cramps, myalgia
Nervous System: | anxiety, hypesthesia of the hand, insomnia, paresthesia, tremor
Special Senses: | eye itch

The following events, considered potentially related to Xopenex, occurred in less than 2% of the treated subjects but at a frequency less than in patients who received placebo: asthma exacerbation, cough increased, wheezing, sweating, and vomiting.

ADVERSE REACTIONS (CHILDREN 6-11 YEARS OLD):

Adverse events reported in ≥2% of patients in any treatment group and more frequently than in patients receiving placebo in a 3-week, controlled clinical trial are listed in Table 5.

Table 5: Most Frequently Reported Adverse Events (≥2% in Any Treatment Group) and Those Reported More Frequently Than in Placebo during the Double-Blind Period (ITT Population, 6-11 Years Old)
 | Percent of Patients
Body System Preferred Term | Placebo (n=59) | Xopenex 0.31 mg (n=66) | Xopenex 0.63 mg (n=67) | Racemic albuterol 1.25 mg (n=64) | Racemic albuterol 2.5 mg (n=60)
Body as a Whole
Abdominal pain | 3.4 | 0 | 1.5 | 3.1 | 6.7
Accidental injury | 3.4 | 6.1 | 4.5 | 3.1 | 5.0
Asthenia | 0 | 3.0 | 3.0 | 1.6 | 1.7
Fever | 5.1 | 9.1 | 3.0 | 1.6 | 6.7
Headache | 8.5 | 7.6 | 11.9 | 9.4 | 3.3
Pain | 3.4 | 3.0 | 1.5 | 4.7 | 6.7
Viral Infection | 5.1 | 7.6 | 9.0 | 4.7 | 8.3
Digestive System
Diarrhea | 0 | 1.5 | 6.0 | 1.6 | 0
Hemic and Lymphatic
Lymphadenopathy | 0 | 3.0 | 0 | 1.6 | 0
Musculoskeletal System
Myalgia | 0 | 0 | 1.5 | 1.6 | 3.3
Respiratory System
Asthma | 5.1 | 9.1 | 9.0 | 6.3 | 10.0
Pharyngitis | 6.8 | 3.0 | 10.4 | 0 | 6.7
Rhinitis | 1.7 | 6.1 | 10.4 | 3.1 | 5.0
Skin and Appendages
Eczema | 0 | 0 | 0 | 0 | 3.3
Rash | 0 | 0 | 7.5 | 1.6 | 0
Urticaria | 0 | 0 | 3.0 | 0 | 0
Special Senses
Otitis Media | 1.7 | 0 | 0 | 0 | 3.3
Note: Subjects may have more than one adverse event per body system and preferred term.

Changes in heart rate, plasma glucose, and serum potassium are shown in Table 6. The clinical significance of these small differences is unknown.

Table 6: Mean Changes from Baseline Heart Rate at 30 Minutes and Glucose and Potassium at 1 Hour after First Dose (Day 1) and Last Dose (Day 21) in Children 6-11 years old
Treatment | Mean Changes (Day 1)
Treatment | Heart Rate (bpm) | Glucose (mg/dL) | Potassium (mEq/L)
Xopenex 0.31 mg, n=66 | 0.8 | 4.9 | –0.31
Xopenex 0.63 mg, n=67 | 6.7 | 5.2 | –0.36
Racemic albuterol 1.25 mg, n=64 | 6.4 | 8.0 | –0.27
Racemic albuterol 2.5 mg, n=60 | 10.9 | 10.8 | –0.56
Placebo, n=59 | –1.8 | 0.6 | –0.05
 | Mean Changes (Day 21)
Treatment | Heart Rate (bpm) | Glucose (mg/dL) | Potassium (mEq/L)
Xopenex 0.31 mg, n= 60 | 0 | 2.6 | –0.32
Xopenex 0.63 mg, n=66 | 3.8 | 5.8 | –0.34
Racemic albuterol 1.25 mg, n= 62 | 5.8 | 1.7 | –0.18
Racemic albuterol 2.5 mg, n= 54 | 5.7 | 11.8 | –0.26
Placebo, n= 55 | –1.7 | 1.1 | –0.04

POSTMARKETING ADVERSE REACTIONS:

In addition to the adverse events reported in clinical trials, the following adverse events have been observed in postapproval use of Xopenex Inhalation Solution. These events have been chosen for inclusion due to their seriousness, their frequency of reporting, or their likely beta-mediated mechanism: angioedema, anaphylaxis, arrhythmias (including atrial fibrillation, supraventricular tachycardia, extrasystoles), asthma, chest pain, cough increased, dyspnea, nausea, nervousness, rash, tachycardia, tremor, urticaria. Because these events have been reported spontaneously from a population of unknown size, estimates of frequency cannot be made.

OVERDOSAGE:

The expected symptoms with overdosage are those of excessive beta-adrenergic receptor stimulation and/or occurrence or exaggeration of any of the symptoms listed under ADVERSE REACTIONS, e.g., seizures, angina, hypertension or hypotension, tachycardia with rates up to 200 beats/min., arrhythmias, nervousness, headache, tremor, dry mouth, palpitation, nausea, dizziness, fatigue, malaise, and sleeplessness. Hypokalemia also may occur. As with all sympathomimetic medications, cardiac arrest and even death may be associated with the abuse of Xopenex Inhalation Solution. Treatment consists of discontinuation of Xopenex Inhalation Solution together with appropriate symptomatic therapy. The judicious use of a cardioselective beta-receptor blocker may be considered, bearing in mind that such medication can produce bronchospasm. There is insufficient evidence to determine if dialysis is beneficial for overdosage of Xopenex Inhalation Solution.

The intravenous median lethal dose of levalbuterol HCl in mice is approximately 66 mg/kg (approximately 70 times the maximum recommended daily inhalation dose of levalbuterol HCl for adults and children on a mg/m^2 basis). The inhalation median lethal dose has not been determined in animals.

DOSAGE AND ADMINISTRATION:

Children 6–11 years old: The recommended dosage of Xopenex (levalbuterol HCl) Inhalation Solution for patients 6–11 years old is 0.31 mg administered three times a day, by nebulization. Routine dosing should not exceed 0.63 mg three times a day.

Adults and Adolescents ≥12 years old: The recommended starting dosage of Xopenex (levalbuterol HCl) Inhalation Solution for patients 12 years of age and older is 0.63 mg administered three times a day, every 6 to 8 hours, by nebulization.

Patients 12 years of age and older with more severe asthma or patients who do not respond adequately to a dose of 0.63 mg of Xopenex Inhalation Solution may benefit from a dosage of 1.25 mg three times a day.

Patients receiving the highest dose of Xopenex Inhalation Solution should be monitored closely for adverse systemic effects, and the risks of such effects should be balanced against the potential for improved efficacy.

The use of Xopenex Inhalation Solution can be continued as medically indicated to control recurring bouts of bronchospasm. During this time, most patients gain optimal benefit from regular use of the inhalation solution.

If a previously effective dosage regimen fails to provide the expected relief, medical advice should be sought immediately, since this is often a sign of seriously worsening asthma that would require reassessment of therapy.

The drug compatibility (physical and chemical), efficacy, and safety of Xopenex Inhalation Solution when mixed with other drugs in a nebulizer have not been established.

The safety and efficacy of Xopenex Inhalation Solution have been established in clinical trials when administered using the PARI LC Jet™ and PARI LC Plus™ nebulizers, and the PARI Master® Dura-Neb® 2000 and Dura-Neb® 3000 compressors. The safety and efficacy of Xopenex Inhalation Solution when administered using other nebulizer systems have not been established.

HOW SUPPLIED:

Xopenex (levalbuterol HCl) Inhalation Solution is supplied in 3 mL unit-dose, low-density polyethylene (LDPE) vials as a clear, colorless, sterile, preservative-free, aqueous solution, in three different strengths of levalbuterol (0.31 mg, 0.63 mg, 1.25 mg). Each strength of Xopenex Inhalation Solution is available in a shelf-carton containing one or more foil pouches, each containing 12 unit-dose LDPE vials.

Xopenex (levalbuterol HCl) Inhalation Solution, 1.25 mg (foil pouch label color red) contains 1.25 mg of levalbuterol (as 1.44 mg of levalbuterol HCl) and is available in cartons of 24 unit-dose LDPE vials (NDC 21695-153-24).

Store Xopenex (levalbuterol HCl) Inhalation Solution in the protective foil pouch at 20-25°C (68-77°F) [see USP Controlled Room Temperature]. Protect from light and excessive heat. Keep unopened vials in the foil pouch. Once the foil pouch is opened, the vials should be used within 2 weeks. Vials removed from the pouch, if not used immediately, should be protected from light and used within 1 week. Discard any vial if the solution is not colorless.

SEPRACOR

Manufactured for:
Sepracor Inc.
Marlborough, MA 01752 USA
For customer service, call 1-888-394-7377.
To report adverse events, call 1-877-737-7226.
For medical information, call 1-800-739-0565.

February 2009
400437R07

Repackaged by:

Rebel Distributors Corp

Thousand Oaks, CA 91320

PHARMACIST — DETACH HERE AND GIVE INSTRUCTIONS TO PATIENT

---------------------------------------------------------------------------------------------------------------

Patient's Instructions for Use

Xopenex®

(levalbuterol HCl)

Inhalation Solution

0.31 mg*, 0.63 mg*, 1.25 mg*
3 mL Unit-Dose Vials

*Potency expressed as levalbuterol

Read complete instructions carefully before using.

Figure 1
Figure 2
Figure 3
Figure 4

1. Open the foil pouch by tearing on the serrated edge along the seam of the pouch. Remove one unit-dose vial for immediate use. Keep the rest of the unused unit-dose vials in the foil pouch to protect them from light.
2. Hold the unit-dose vial in your hands as shown in Figure 2.
3. Ensure your thumb and finger cover the twist-off tabs below the “X” top (Figure 2).
4. Twist the body of the unit-dose vial while holding the top firmly between your thumb and finger to open the vial.
5. Discard the top and squeeze the entire contents into the nebulizer reservoir.
6. Connect the nebulizer reservoir to the mouthpiece or face mask (Figure 3).
7. Connect the nebulizer to the compressor.
8. Sit in a comfortable, upright position. Place the mouthpiece in your mouth (Figure 4) (or put on the face mask) and turn on the compressor.
9. Breathe as calmly, deeply, and evenly as possible until no more mist is formed in the nebulizer reservoir (about 5 to 15 minutes). At this point, the treatment is finished.
10. Clean the nebulizer (see manufacturer's instructions).

Note: Xopenex (levalbuterol HCl) Inhalation Solution should be used in a nebulizer only under the direction of a physician. More frequent administration or higher doses are not recommended without first discussing with your doctor. This solution should not be injected or administered orally. Protect from light and excessive heat. Store in the protective foil pouch at 20-25°C (68-77°F) [see USP Controlled Room Temperature]. Keep unopened vials in the foil pouch. Once the foil pouch is opened, the vials should be used within 2 weeks. Vials removed from the pouch, if not used immediately, should be protected from light and used within 1 week. Discard any vial if the solution is not colorless.

The safety and effectiveness of Xopenex Inhalation Solution have not been determined when one or more drugs are mixed with it in a nebulizer. Check with your doctor before mixing any medications in your nebulizer.

SEPRACOR
Manufactured for:
Sepracor Inc.
Marlborough, MA 01752 USA
For customer service, call 1-888-394-7377.
To report adverse events, call 1-877-737-7226.
For medical information, call 1-800-739-0565.

February 2009

400437R07

Repackaged by:

Rebel Distributors Corp

Thousand Oaks, CA 91320

PRINCIPAL DISPLAY PANEL - 1.25 TRADE CARTON LABEL

NDC 21695-153-24

1.25 mg

Xopenex®

(levalbuterol HCl)

Inhalation Solution,

1.25 mg/3 mL*

*Potency expressed as levalbuterol

For Oral Inhalation Only. Sterile Unit-Dose Vial

24 x 3 mL Sterile Unit-Dose Vials

Repackaged by:

Rebel Distributors Corp

Thousand Oaks, CA 91320